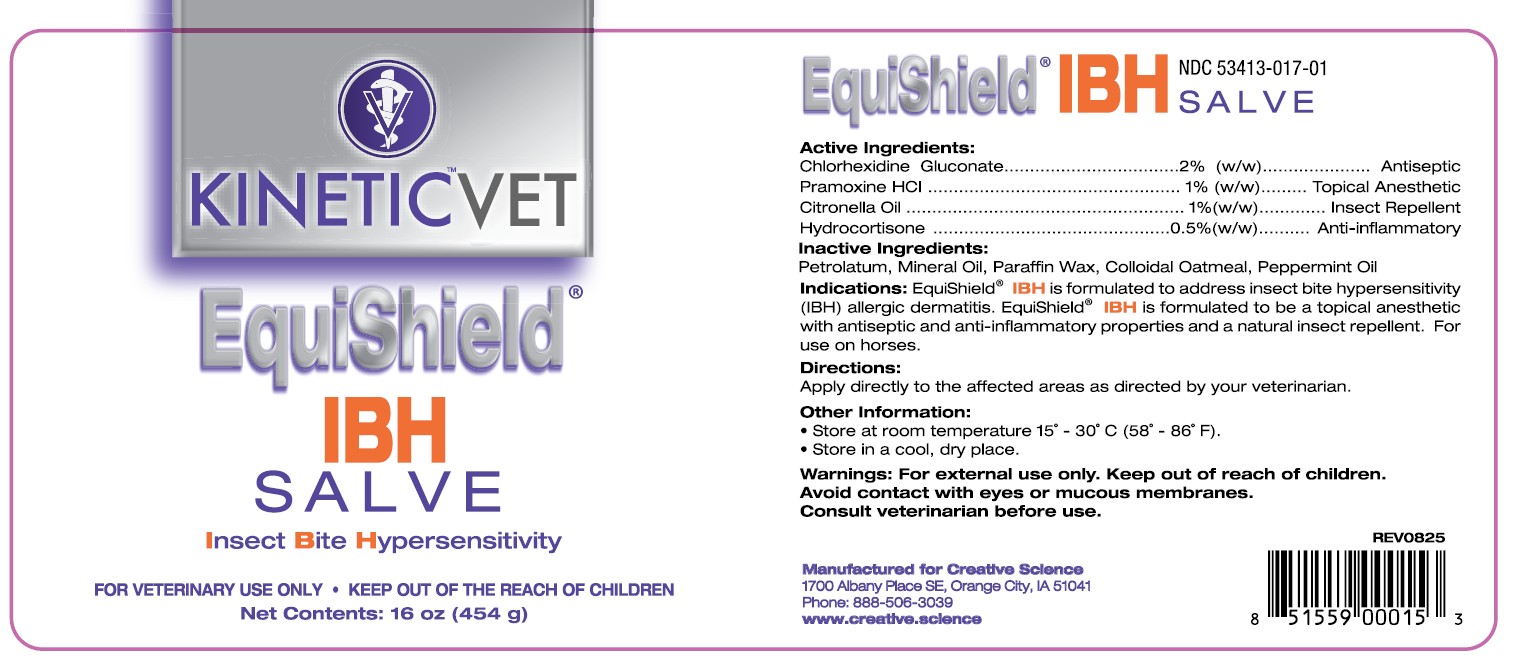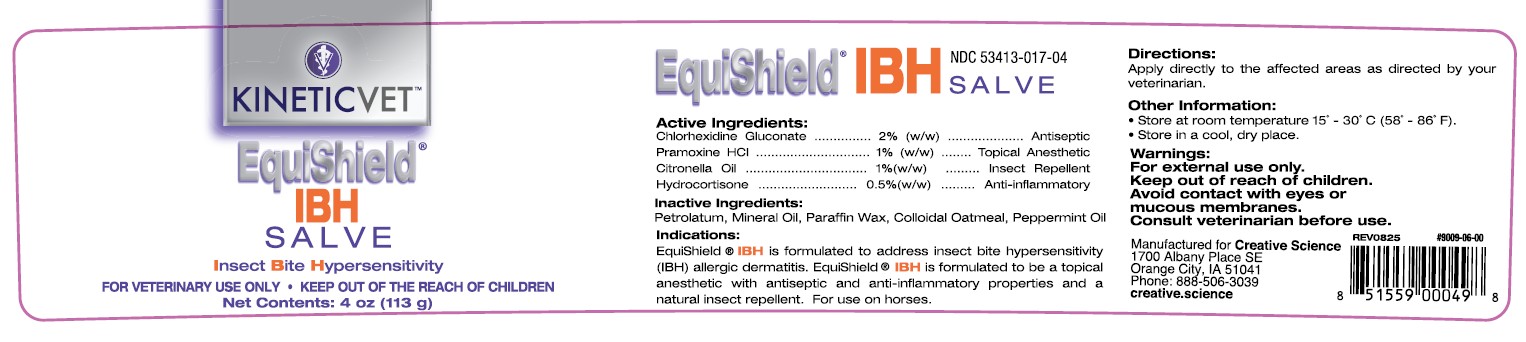 DRUG LABEL: EquiShield IBH Salve
NDC: 53413-017 | Form: SALVE
Manufacturer: Creative Science
Category: animal | Type: OTC ANIMAL DRUG LABEL
Date: 20251208

ACTIVE INGREDIENTS: CHLORHEXIDINE GLUCONATE 2 g/100 g; PRAMOXINE HYDROCHLORIDE 1 g/100 g; CITRONELLA OIL 1 g/100 g; HYDROCORTISONE 0.5 g/100 g

EquiShield IBH Salve

NDC 53413-017-04 4 oz

NDC 53413-017-01 16 oz

Active Ingredients:

Chlorhexidine Gluconate........2% (w/w)....................Antiseptic

Pramoxine HCL.....................1% (w/w).........Topical Anesthetic

Citronella Oil....................... 1% (w/w)............Insect Repellent

Hydrocortisone .................0.5% (w/w).........Anti-Inflammatory

Inactive Ingredients:

Petrolatum, Mineral Oil, Paraffin Wax, Colloidal Oatmeal, Peppermint Oil

Indications:

EquiShield® IBH Salve is formulated to address insect bite hypersensitivity (IBH) allergic dermatitis. EquiShield® IBH is formulated to be a topical anesthetic with antiseptic and anti-inflammatory properties and a natural insect repellant. For use on horses.

Directions:

Apply directly to the affected areas as directed by your veterinarian.

Other Information:

• Store at room temperature 15˚ - 30˚C (58˚ - 86˚F).
• Store in a cool, dry place.

Warnings:

For external use only.

Keep out of reach of children.

Avoid contact with eyes or mucous membranes.

Consult veterinarian before use.

REV 0825

#9009-06-00 UPC 851559000498 4 oz

UPC 851559000153 16 oz

Manufactured for Creative Science

1700 Albany Place SE, Orange City, IA 51041

Phone: 888-506-3039

www.creative.science

KINETICVET™

EquiShield® IBH SALVE

Insect Bite Hypersensitivity

FOR VETERINARY USE ONLY • KEEP OUT OF THE REACH OF CHILDREN

Net Contents: 4 oz (113 g)

EquiShield® IBH SALVE

Insect Bite Hypersensitivity

FOR VETERINARY USE ONLY • KEEP OUT OF THE REACH OF CHILDREN

Net Contents: 16 oz (454 g)